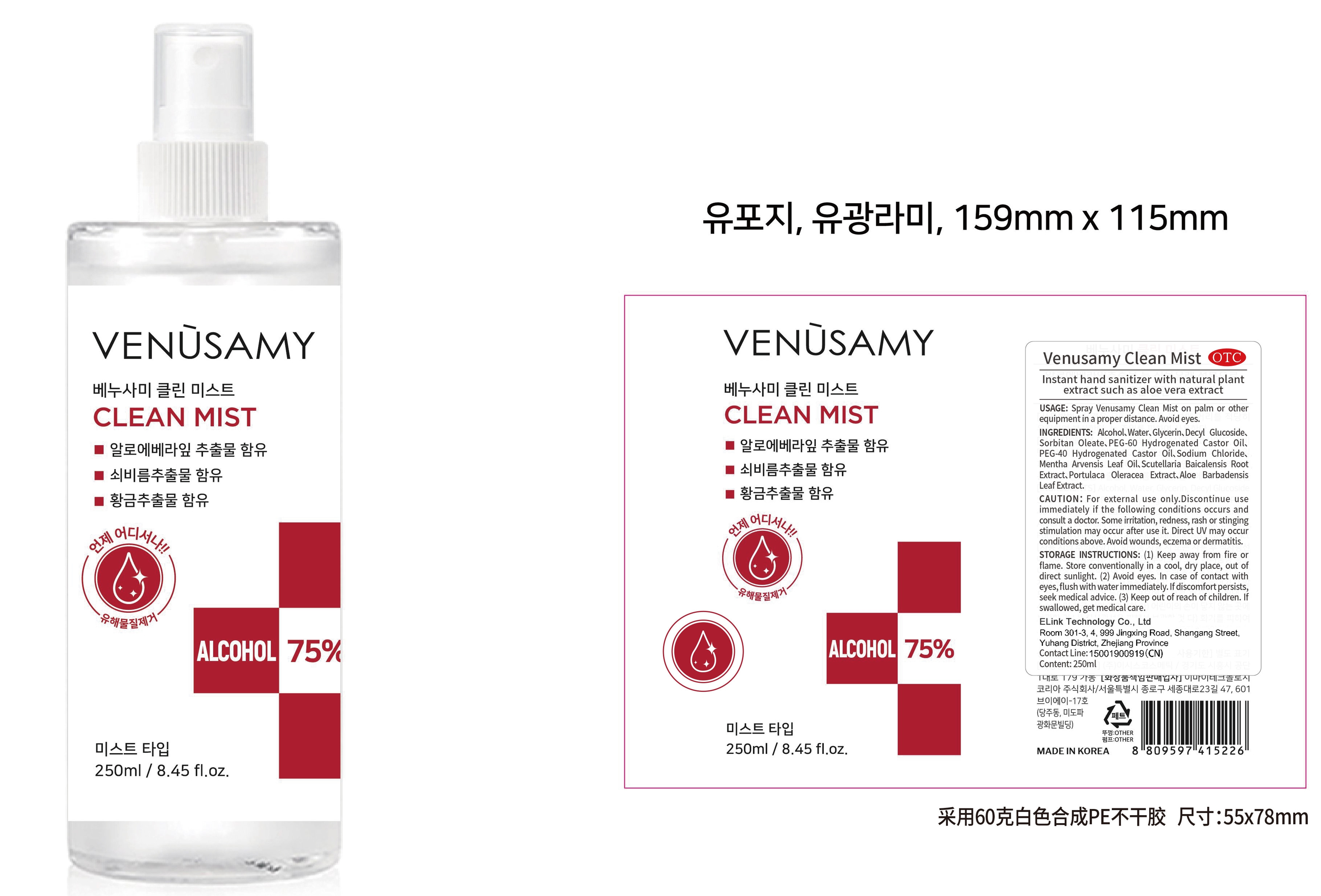 DRUG LABEL: Venusamy clean mist
NDC: 55418-004 | Form: LIQUID
Manufacturer: ELink Technology Co., Ltd.
Category: otc | Type: HUMAN OTC DRUG LABEL
Date: 20200424

ACTIVE INGREDIENTS: ALCOHOL 187.5 mL/250 mL
INACTIVE INGREDIENTS: PEG-60 HYDROGENATED CASTOR OIL; SODIUM CHLORIDE; SCUTELLARIA BAICALENSIS ROOT; MENTHA ARVENSIS LEAF OIL; WATER; GLYCERIN; SORBITAN MONOOLEATE; ALOE VERA LEAF; DECYL GLUCOSIDE; PURSLANE; POLYOXYL 40 HYDROGENATED CASTOR OIL

DOSAGE AND ADMINISTRATION

Keep away from fire or flame. Store conventionally in a Cool dry place,out of direct sunlight.

INACTIVE INGREDIENT

Water

Glycerin

Decyl Glucoside

Sorbitan Oleate

PEG-60 Hydrogenated Castor Oil

PEG-40 Hydrogenated Castor Oil

Sodium Chloride

Mentha Arvensis Leaf Oil

Scutellaria Baicalensis Root Extract

Portulaca Oleracea Extract

Aloe Barbadensis Leaf Extract

INDICATIONS AND USAGE

Spray Venusamy Cean Mist on palm of other equipment in a proper distance. Avoid eyes.

ACTIVE INGREDIENT

Alcohol

keep out of children

PURPOSE

Disinfection
Sterilization

WARNINGS

For extermal use only,Discontinue use immediatelyif the fllwing conditions occurs and consult a doctor. Some rritation, redness, rash or
stinging stimulation may occur ater u5 it. Direct UV may occur conditions above. Avold wounds,